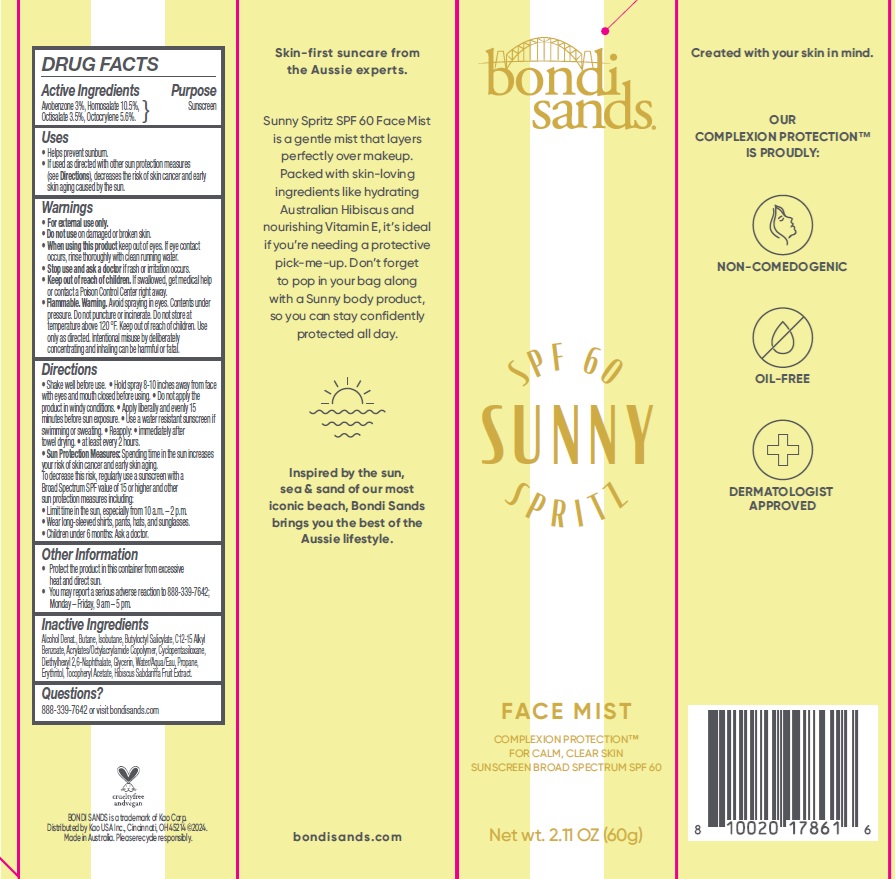 DRUG LABEL: Bondi Sands SPF 60 Sunny Spritz Face Mist
NDC: 79950-016 | Form: AEROSOL, SPRAY
Manufacturer: BONDI SANDS (USA) INC.
Category: otc | Type: HUMAN OTC DRUG LABEL
Date: 20250106

ACTIVE INGREDIENTS: OCTISALATE 35 mg/1 g; OCTOCRYLENE 56 mg/1 g; AVOBENZONE 30 mg/1 g; HOMOSALATE 105 mg/1 g
INACTIVE INGREDIENTS: ALCOHOL; BUTANE; CYCLOPENTASILOXANE; ERYTHRITOL; .ALPHA.-TOCOPHEROL ACETATE; DIETHYLHEXYL 2,6-NAPHTHALATE; WATER; BUTYLOCTYL SALICYLATE; C12-15 ALKYL BENZOATE; GLYCERIN; PROPANE; ISOBUTANE; ACRYLATES/OCTYLACRYLAMIDE COPOLYMER (75000 MW)

Bondi Sands SPF 60 Sunny Spritz Face Mist

Active Ingredients

Avobenzone 3%

Homosalate 10.5%

Octisalate 3.5%

Octocrylene 5.6%

Purpose

Sunscreen

Uses

- Helps prevent sunburn.
- If used as directed with other sun protection measures (see Directions), decreases the risk of skin cancer and early skin aging caused by the sun.

Warnings

- For external use only.

Do not use

on damaged or broken skin.

When using this product

keep out of eyes. If eye contact occurs, rinse thoroughly with clean running water.

Stop use and ask a doctor

if rash or irritation occurs.

Keep out of reach of children.

If swallowed, get medical help or contact a Poison Control Center right away.

Flammable. Warning.

Avoid spraying in eyes. Contents under pressure. Do not puncture or incinerate. Do not store at temperature above 120F. Keep out of reach of children. Use only as directed. Intentional misuse by deliberately concentrating and inhaling can be harmful or fatal.

Directions

- Shake well before use.
- Hold spray 8-10 inches away from face with eyes and mouth closed before using.
- Do not apply the product in windy conditions.
- Apply liberally and evenly 15 minutes before sun exposure.
- Use a water resistant sunscreen if swimming or sweating.
- Reapply:
- immediately after towel drying.
- at least every 2 hours.
- Sun Protection Measures: Spending time in the sun increases your risk of skin cancer and early skin aging. To decrease this risk, regularly use a sunscreen with a Broad Spectrum SPF value of 15 or higher and other sun protection measures including:
- Limit time in the sun, especially from 10 a.m. - 2 p.m.
- Wear long-sleeved shirts, pants, hats, and sunglasses.
- Children under 6 months: Ask a doctor.

Other Information

- Protect the product in this container from excessive heat and direct sun.
- You may report a serious adverse reaction to 888-339-7642; Monday-Friday, 9 am - 5 pm.

Inactive Ingredients

Alcohol Denat., Butane, Isobutane, Butyloctyl Salicylate, C12-15 Alkyl Benzoate, Acrylates/Octylacrylamide Copolymer, Cyclopentasiloxane, Diethylhexyl 2,6-Naphthalate, Glycerin, Water/Aqua/Eau, Propane, Erythritol, Tocopheryl Acetate, Hibiscus Sabdariffa Fruit Extract

Questions?

888-339-7642 or visit bondisands.com